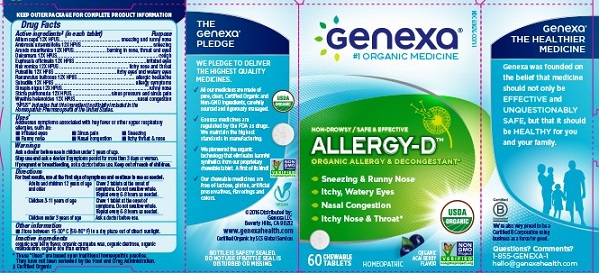 DRUG LABEL: Allergy D
NDC: 10564-0071 | Form: TABLET, CHEWABLE
Manufacturer: Bershtel Enterprises LLC
Category: homeopathic | Type: HUMAN OTC DRUG LABEL
Date: 20180607

ACTIVE INGREDIENTS: PULSATILLA PRATENSIS 12 [hp_X]/1 1; SCHOENOCAULON OFFICINALE SEED 12 [hp_X]/1 1; SOLANUM DULCAMARA STEM 12 [hp_X]/1 1; EUPHRASIA STRICTA 12 [hp_X]/1 1; ONION 12 [hp_X]/1 1; AMBROSIA ARTEMISIIFOLIA 12 [hp_X]/1 1; STRYCHNOS NUX-VOMICA SEED 12 [hp_X]/1 1; ARUNDO PLINIANA ROOT 12 [hp_X]/1 1; RANUNCULUS BULBOSUS 12 [hp_X]/1 1; WYETHIA HELENIOIDES ROOT 12 [hp_X]/1 1; BLACK MUSTARD SEED 12 [hp_X]/1 1; LOBARIA PULMONARIA 12 [hp_X]/1 1
INACTIVE INGREDIENTS: RICE BRAN; DEXTROSE; CARNAUBA WAX; MALTODEXTRIN

Active ingredients (in each tablet)

Allium cepa 12X HPUS

Ambrosia artemisiifolia 12X HPUS

Arundo mauritanica 12X HPUS

Dulcamara 12X HPUS

Euphrasia officinalis 12X HPUS

Nux vomica 12X HPUS

Pulsatilla 12X HPUS

Ranunculus bulbosus 12X HPUS

Sabadilla 12X HPUS

Sinapis nigra 12X HPUS

Sticta pulmonaria 12X HPUS

Wyethia helenoides 12X HPUS

"HPUS" indicates that this ingredient is officially included in the Homeopathic Pharmacopoeia of the United States.

Purpose

sneezing and runny nose

sneezing

burning in nose, throat and eyes

cough

irritated eyes

itchy nose and throat

itchy eyes and watery eyes

allergic headache

allergy symptoms

runny nose

sinus pressure and sinus pain

nasal congestion

Uses

Irratated eyes, sinus pain, sneezing, runny nose, nasal congestion, itchy throat and nose

Ask a doctor before use in children under 3 years of age.

Stop use and ask a doctor if symptoms persist for more than 3 days or worsen.

PREGNANCY OR BREAST FEEDING

If pregnant or breastfeeding, ask a doctor before use.

Keep out of reach of children.

Directions

For best results, use at first sign of symptoms and continue to use as needed.

Adults and children 12 years of age and older. Chew 2 tablets at the onset of symptoms. Do not swallow whole.Repeat every 4-6 hours as needed.

Children 3-11 yers of age. Chew 1 tablets at the onset of symptoms. Do not swallow whole.Repeat every 4-6 hours as needed.

Children under 3 years of age. Ask a Doctor before use.

STORAGE AND HANDLING

Store between 15-30° C (59-86° F) in a dry place out of direct sunlight.

Inactive ingredients

organic acai berry flavor, organic carnauba wax, organic dextrose, organic maltodextrin, organic rice bran extract

Do not use if packaging is not sealed.

Do not use if it appears to have been tampered with.